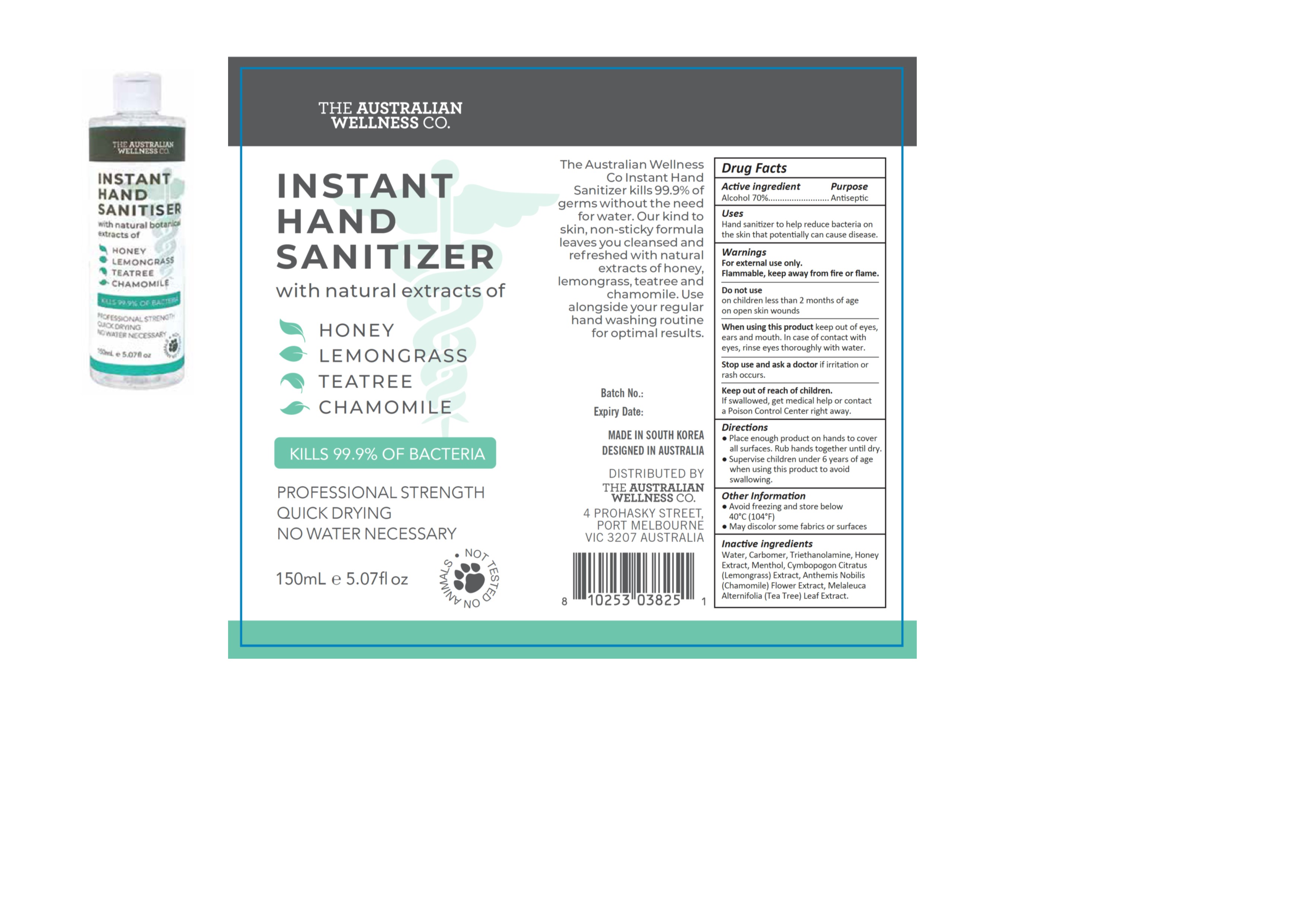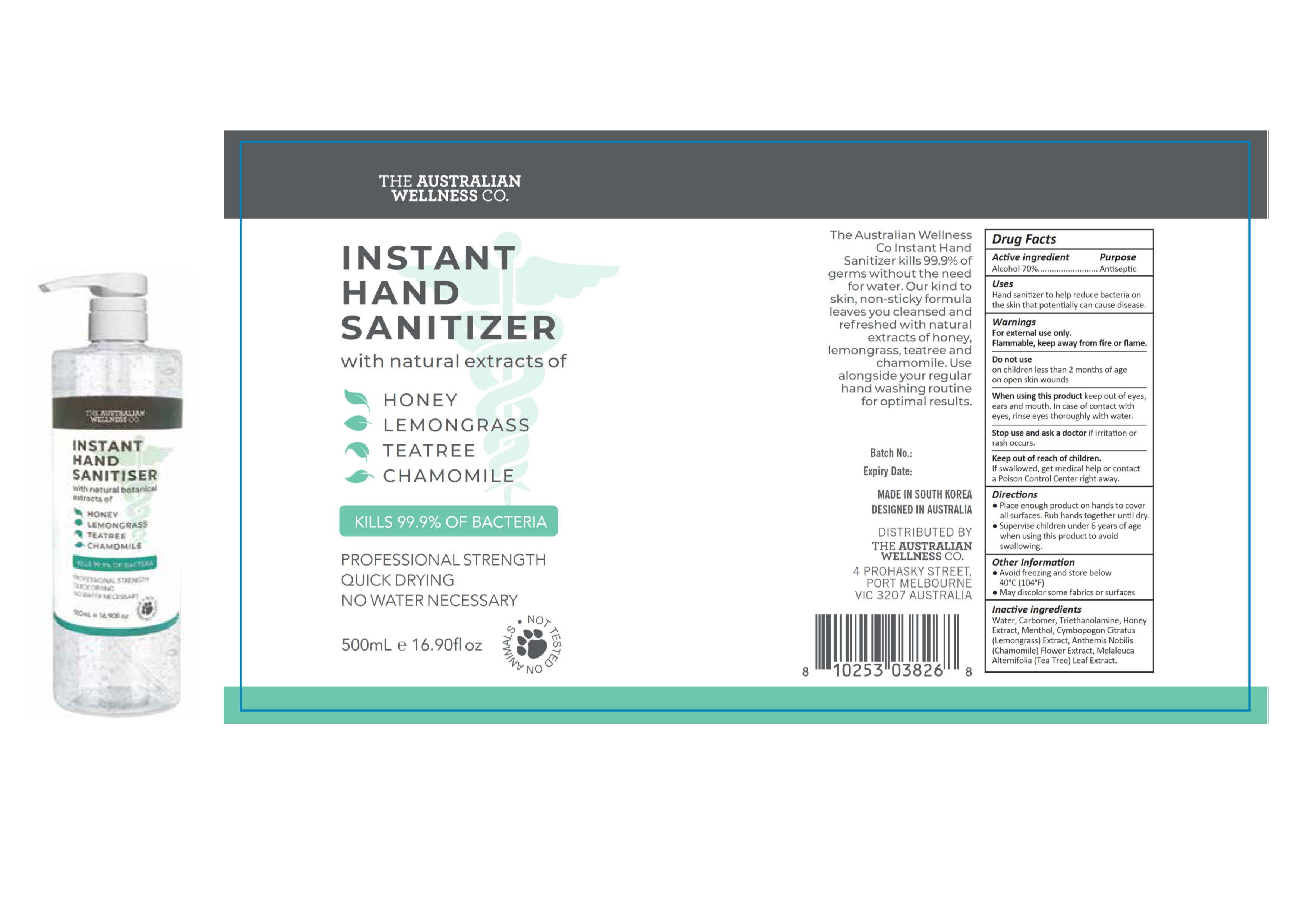 DRUG LABEL: Hand Sanitizer
NDC: 74443-010 | Form: GEL
Manufacturer: VANILLA SUGAR PTY LTD
Category: otc | Type: HUMAN OTC DRUG LABEL
Date: 20200401

ACTIVE INGREDIENTS: ALCOHOL 70 g/100 mL
INACTIVE INGREDIENTS: MELALEUCA ALTERNIFOLIA LEAF; CARBOMER 934; TROLAMINE; WATER; CYMBOPOGON CITRATUS WHOLE; HONEY; CHAMOMILE; MENTHOL

Active Ingredient(s)

Alcohol 70%. Purpose: Antiseptic

Purpose

Antiseptic, Hand Sanitizer

Use

Hand Sanitizer to help reduce bacteria on the skin that potentially can cause disease.

Warnings

For external use only. Flammable. Keep away from heat or flame

Do not use

- in children less than 2 months of age
- on open skin wounds

When using this product keep out of eyes, ears, and mouth. In case of contact with eyes, rinse eyes thoroughly with water.
Stop use and ask a doctor if irritation or rash occurs.
Keep out of reach of children. If swallowed, get medical help or contact a Poison Control Center right away.

Stop use and ask a doctor if irritation or rash occurs. These may be signs of a serious condition.

Keep out of reach of children. If swallowed, get medical help or contact a Poison Control Center right away.

Directions

- Place enough product on hands to cover all surfaces. Rub hands together until dry.
- Supervise children under 6 years of age when using this product to avoid swallowing.

Other information

- Avoid freezing and store below above 40ºC (104ºF)
- May discolor some fabrics or surfaces

Inactive ingredients

Water, Carbomer, Triethanolamine, Honey Extract, Menthol, Cymbopogon Citratus (Lemongrass) Extract, Anthemis Nobilis (Chamomile) Flower Extract, Melaleuca Alternifolia (Tea Tree) Leaf Extract.

Package Label - Principal Display Panel

150 mL NDC: 74443-010-15

500 mL NDC: 74443-010-50